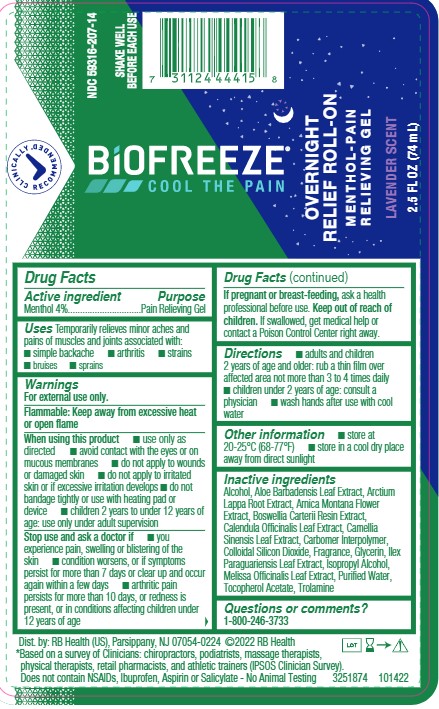 DRUG LABEL: Biofreeze Overnight Roll-on
NDC: 59316-207 | Form: GEL
Manufacturer: RB Health (US) LLC
Category: otc | Type: HUMAN OTC DRUG LABEL
Date: 20241227

ACTIVE INGREDIENTS: MENTHOL 40 mg/1 mL
INACTIVE INGREDIENTS: CALENDULA OFFICINALIS FLOWER; GLYCERIN; GREEN TEA LEAF; FRANKINCENSE; CARBOMER INTERPOLYMER TYPE A (ALLYL SUCROSE CROSSLINKED); MELISSA OFFICINALIS LEAF; ALCOHOL; ARNICA MONTANA FLOWER; ALOE VERA LEAF; ARCTIUM LAPPA ROOT; ISOPROPYL ALCOHOL; WATER; SILICON DIOXIDE; ILEX PARAGUARIENSIS LEAF; .ALPHA.-TOCOPHEROL ACETATE; TROLAMINE

BiOFREEZE ® Overnight Roll-on

Active

Mentol USP 4%

Purpose

Pain Relieving Gel

Uses

Temporarily relieves minor aches and pains of muscles and joints associated with:

■simple backache

■arthritis

■strains

■bruises

■sprains

Warnings

For external use only.

Flammable: Keep away from excessive heat or open flame

When using this product:

■use only as directed ■avoid contact with the eyes or on mucous membranes ■do not apply to wounds or damaged skin ■do not apply to irritated skin or if excessive irritation develops ■do not bandage tightly or use with heating pad or device ■children 2 years to under 12 years of age: use only under adult supervision

Stop use and ask a doctor if:

■ you experience pain, swelling or blistering of the skin ■ condition worsens, or if symptoms persist for more than 7 days or clear up and occur again within a few days ■arthritic pain persists for more than 10 days, or redness is present, or in conditions affecting children under 12 years of age

If pregnant or breast-feeding:

■ ask a health professional before use.

Keep out of reach of children:

- If swallowed, get medical help or contact a Poison Control Center right away.

Directions

■ adults and children 2 years of age and older:

rub a thin film over affected area not more than 3 to 4 times daily

■children under 2 years of age: consult a physician

■wash hands after use with cool water

Other Information

■store at 20-25°C (68-77°F)

■store in a cool dry place away from direct sunlight

Inactive Ingredients

Alcohol, Aloe Barbadensis Leaf Extract, Arctium Lappa Root Extract, Arnica Montana Flower Extract, Boswellia Carterii Resin Extract, Calendula Officinalis Leaf Extract, Camellia Sinensis Leaf Extract, Carbomer Interpolymer, Colloidal Silicon Dioxide, Fragrance, Glycerin, Ilex Paraguariensis Leaf Extract, Isopropyl Alcohol, Melissa Officinalis Leaf Extract, Purified Water, Tocopherol Acetate, Trolamine

Questions or Comments

1-800-246-3733

SPL UNCLASSIFIED SECTION

Dist. by: RB Health (US), Parsippany, NJ 07054-0224

Principal Display Panel - 74 mL Bottle Label

CLINICALLY RECOMMENDED

NDC 59316-207-14

BIOFREEZE

COOL THE PAIN

ROLL-ON

MENTHOL- PAIN RELIEVING GEL

2.5 FL OZ (74mL)

SHAKE WELL BEFORE EACH USE